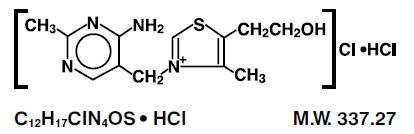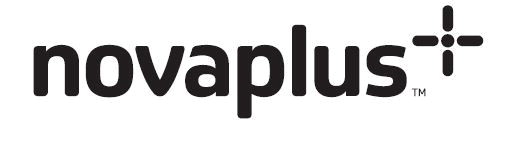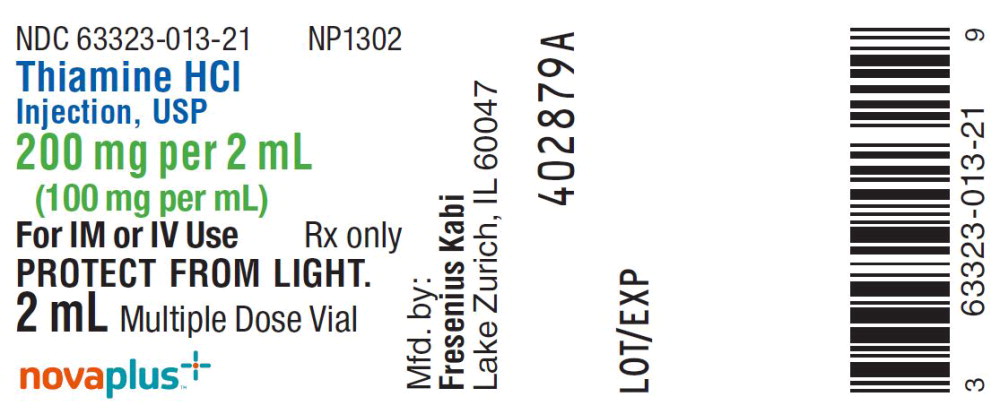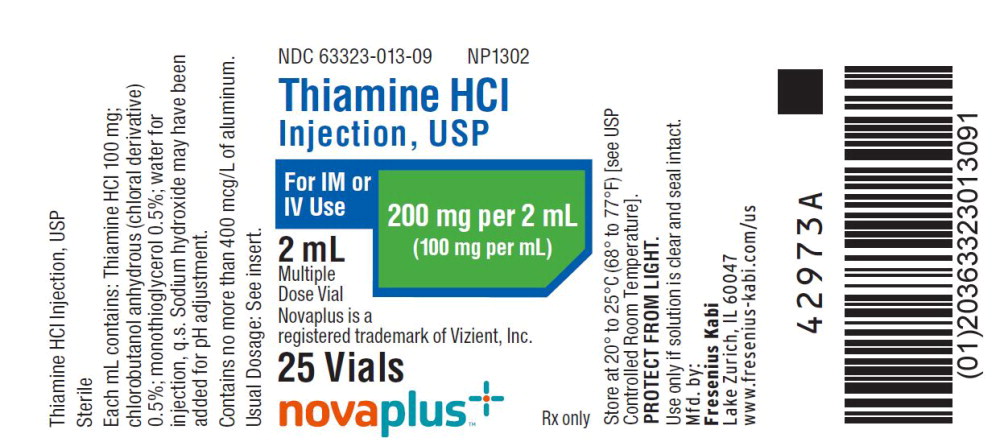 DRUG LABEL: Thiamine
NDC: 63323-013 | Form: INJECTION, SOLUTION
Manufacturer: Fresenius Kabi USA, LLC
Category: prescription | Type: HUMAN PRESCRIPTION DRUG LABEL
Date: 20260114

ACTIVE INGREDIENTS: THIAMINE HYDROCHLORIDE 100 mg/1 mL
INACTIVE INGREDIENTS: CHLOROBUTANOL; MONOTHIOGLYCEROL; SODIUM HYDROXIDE

Thiamine Hydrochloride Injection, USP

DESCRIPTION

Rx only

DESCRIPTION

Thiamine Hydrochloride Injection, USP is a sterile solution of thiamine hydrochloride in Water for Injection for intramuscular (IM) or slow intravenous (IV) administration.

Each mL contains: Thiamine hydrochloride 100 mg; chlorobutanol anhydrous (chloral derivative) 0.5%; monothioglycerol 0.5%; water for injection, q.s. Sodium hydroxide may have been added for pH adjustment (2.5 to 4.5).

Thiamine hydrochloride, or vitamin B1, occurs as white crystals or crystalline powder that usually has a slight characteristic odor. Freely soluble in water; soluble in glycerin; slightly soluble in alcohol; insoluble in ether and benzene. Thiamine is rapidly destroyed in neutral or alkaline solutions but is stable in the dry state. It is reasonably stable to heat in acid solution.

The chemical name of thiamine hydrochloride is thiazolium,3-[(4-amino-2-methyl-5-pyrimidinyl)methyl]-5-(2-hydroxyethyl)-4-methylchloride, monohydrochloride and it has the following structural formula:

CLINICAL PHARMACOLOGY

The water soluble vitamins are widely distributed in both plants and animals. They are absorbed in man by both diffusion and active transport mechanisms. These vitamins are structurally diverse (derivatives of sugar, pyridine, purines, pyrimidine, organic acid complexes and nucleotide complex) and act as coenzymes, as oxidation-reduction agents, possibly as mitochondrial agents. Metabolism is rapid, and the excess is excreted in the urine.

Thiamine is distributed in all tissues. The highest concentrations occur in liver, brain, kidney and heart. When thiamine intake is greatly in excess of need, tissue stores increase two to three times. If intake is insufficient, tissues become depleted of their vitamin content. Absorption of thiamine following IM administration is rapid and complete.

Thiamine combines with adenosine triphosphate (ATP) to form thiamine pyrophosphate, also known as cocarboxylase, a coenzyme. Its role in carbohydrate metabolism is the decarboxylation of pyruvic acid in the blood and α-ketoacids to acetaldehyde and carbon dioxide. Increased levels of pyruvic acid in the blood indicate vitamin B1 deficiency.

The requirement for thiamine is greater when the carbohydrate content of the diet is raised. Body depletion of vitamin B1 can occur after approximately three weeks of total absence of thiamine in the diet.

INDICATIONS AND USAGE

Thiamine hydrochloride injection is effective for the treatment of thiamine deficiency or beriberi whether of the dry (major symptoms related to the nervous system) or wet (major symptoms related to the cardiovascular system) variety. Thiamine hydrochloride injection should be used where rapid restoration of thiamine is necessary, as in Wernicke’s encephalopathy, infantile beriberi with acute collapse, cardiovascular disease due to thiamine deficiency, or neuritis of pregnancy if vomiting is severe. It is also indicated when giving IV dextrose to individuals with marginal thiamine status to avoid precipitation of heart failure.

Thiamine hydrochloride injection is also indicated in patients with established thiamine deficiency who cannot take thiamine orally due to coexisting severe anorexia, nausea, vomiting, or malabsorption. Thiamine hydrochloride injection is not usually indicated for conditions of decreased oral intake or decreased gastrointestinal absorption, because multiple vitamins should usually be given.

CONTRAINDICATIONS

A history of sensitivity to thiamine or to any of the ingredients in this drug is a contraindication. (See WARNINGS for further information.)

WARNINGS

WARNING: This product contains aluminum that may be toxic. Aluminum may reach toxic levels with prolonged parenteral administration if kidney function is impaired. Premature neonates are particularly at risk because their kidneys are immature, and they require large amounts of calcium and phosphate solutions, which contain aluminum.

Research indicates that patients with impaired kidney function, including premature neonates, who receive parenteral levels of aluminum at greater than 4 to 5 mcg/kg/day accumulate aluminum at levels associated with central nervous system and bone toxicity. Tissue loading may occur at even lower rates of administration.

Serious hypersensitivity/anaphylactic reactions can occur, especially after repeated administration. Deaths have resulted from IV or IM administration of thiamine (see ADVERSE REACTIONS).

Routine testing for hypersensitivity, in many cases, may not detect hypersensitivity. Nevertheless, a skin test should be performed on patients who are suspected of drug allergies or previous reactions to thiamine, and any positive responders should not receive thiamine by injection.

If hypersensitivity to thiamine is suspected (based on history of drug allergy or occurrence of adverse reactions after thiamine administration), administer one-hundredth of the dose intradermally and observe for 30 minutes. If no reaction occurs, full dose can be given; the patient should be observed for at least 30 minutes after injection. Be prepared to treat anaphylactic reactions regardless of the precautions taken.

Treatment of anaphylactic reactions includes maintaining a patent airway and the use of epinephrine, oxygen, vasopressors, steroids and antihistamines.

PRECAUTIONS

General

Simple vitamin B1 deficiency is rare. Multiple vitamin deficiencies should be suspected in any case of dietary inadequacy.

Information for Patients

The patient should be advised as to proper dietary habits during treatment so that relapses will be less likely to occur with reduction in dosage or cessation of injection therapy.

Usage in Pregnancy

Pregnancy Category A–Studies in pregnant women have not shown that thiamine hydrochloride increases the risk of fetal abnormalities if administered during pregnancy. If the drug is used during pregnancy, the possibility of fetal harm appears remote. Because studies cannot rule out the possibility of harm however, thiamine hydrochloride should be used during pregnancy only if clearly needed.

Nursing Mothers

It is not known whether this drug is excreted in human milk. Because many drugs are excreted in human milk, caution should be exercised when thiamine hydrochloride is administered to a nursing mother.

ADVERSE REACTIONS

To report SUSPECTED ADVERSE REACTIONS, contact Fresenius Kabi USA, LLC at 1-800-551-7176 or FDA at 1-800-FDA-1088 or www.fda.gov/medwatch.

An occasional individual may develop a hypersensitivity or life-threatening anaphylactic reaction to thiamine, especially after repeated injections. Collapse and death have been reported. A feeling of warmth, pruritus, urticaria, weakness, sweating, nausea, restlessness, tightness of the throat, angioneurotic edema, cyanosis, pulmonary edema, and hemorrhage into the gastrointestinal tract have also been reported. Some tenderness and induration may follow IM use (see WARNINGS).

OVERDOSAGE

Parenteral doses of 100 to 500 mg singly have been administered without toxic effects. However, dosages exceeding 30 mg three times a day are not utilized effectively.

When the body tissues are saturated with thiamine, it is excreted in the urine as pyrimidine. As the intake of thiamine is further increased, it appears unchanged in the urine.

DOSAGE AND ADMINISTRATION

“Wet” beriberi with myocardial failure must be treated as an emergency cardiac condition, and thiamine must be administered slowly by the IV route in this situation (see WARNINGS).

In the treatment of beriberi, 10 to 20 mg of thiamine hydrochloride are given IM three times daily for as long as two weeks. (See WARNINGS regarding repeated injections of thiamine.) An oral therapeutic multivitamin preparation containing 5 to 10 mg thiamine, administered daily for one month, is recommended to achieve body tissue saturation.

Infantile beriberi that is mild may respond to oral therapy, but if collapse occurs, doses of 25 mg may cautiously be given IV.

Poor dietary habits should be corrected and an abundant and well-balanced dietary intake should be prescribed.

Patients with neuritis of pregnancy in whom vomiting is severe enough to preclude adequate oral therapy should receive 5 to 10 mg of thiamine hydrochloride IM daily.

In the treatment of Wernicke-Korsakoff syndrome, thiamine hydrochloride has been administered IV in an initial dose of 100 mg, followed by IM doses of 50 to 100 mg daily until the patient is consuming a regular, balanced diet. (See WARNINGS regarding repeated injections of thiamine.)

Patients with marginal thiamine status to whom dextrose is being administered should receive 100 mg thiamine hydrochloride in each of the first few liters of IV fluid to avoid precipitating heart failure.

Parenteral drug products should be inspected visually for particulate matter and discoloration prior to administration, whenever solution and container permit.

HOW SUPPLIED

Thiamine Hydrochloride Injection, USP is supplied as follows:

Product Code | Unit of Sale | Strength | Each
NP1302 | NDC 63323-013-09 Unit of 25 | 200 mg per 2 mL (100 mg per mL) | NDC 63323-013-21 2 mL Multiple Dose Vial

Store at 20° to 25°C (68° to 77°F)[see USP Controlled Room Temperature].

PROTECT FROM LIGHT.

Use only if solution is clear and seal intact.

Novaplus is a registered trademark of Vizient, Inc.

Manufactured by:

Fresenius Kabi
Lake Zurich, IL 60047

www.fresenius-kabi.com/us

451355A

Revised: October 2019

PACKAGE LABEL

PACKAGE LABEL - PRINCIPAL DISPLAY - Thiamine 2 mL Multiple Dose Vial Label

NDC 63323-013-21 NP1302

Thiamine HCl Injection, USP

200 mg per 2 mL
(100 mg per mL)

For IM or IV Use

Rx only

PROTECT FROM LIGHT.

2 mL Multiple Dose Vial

PACKAGE LABEL - PRINCIPAL DISPLAY - Thiamine 2 mL Multiple Dose Vial Tray Label

NDC 63323-013-09 NP1302

Thiamine HCl Injection, USP

200 mg per 2 mL
(100 mg per mL)

For IM or IV Use

2 mL Multiple Dose Vial

25 Vials

Rx only